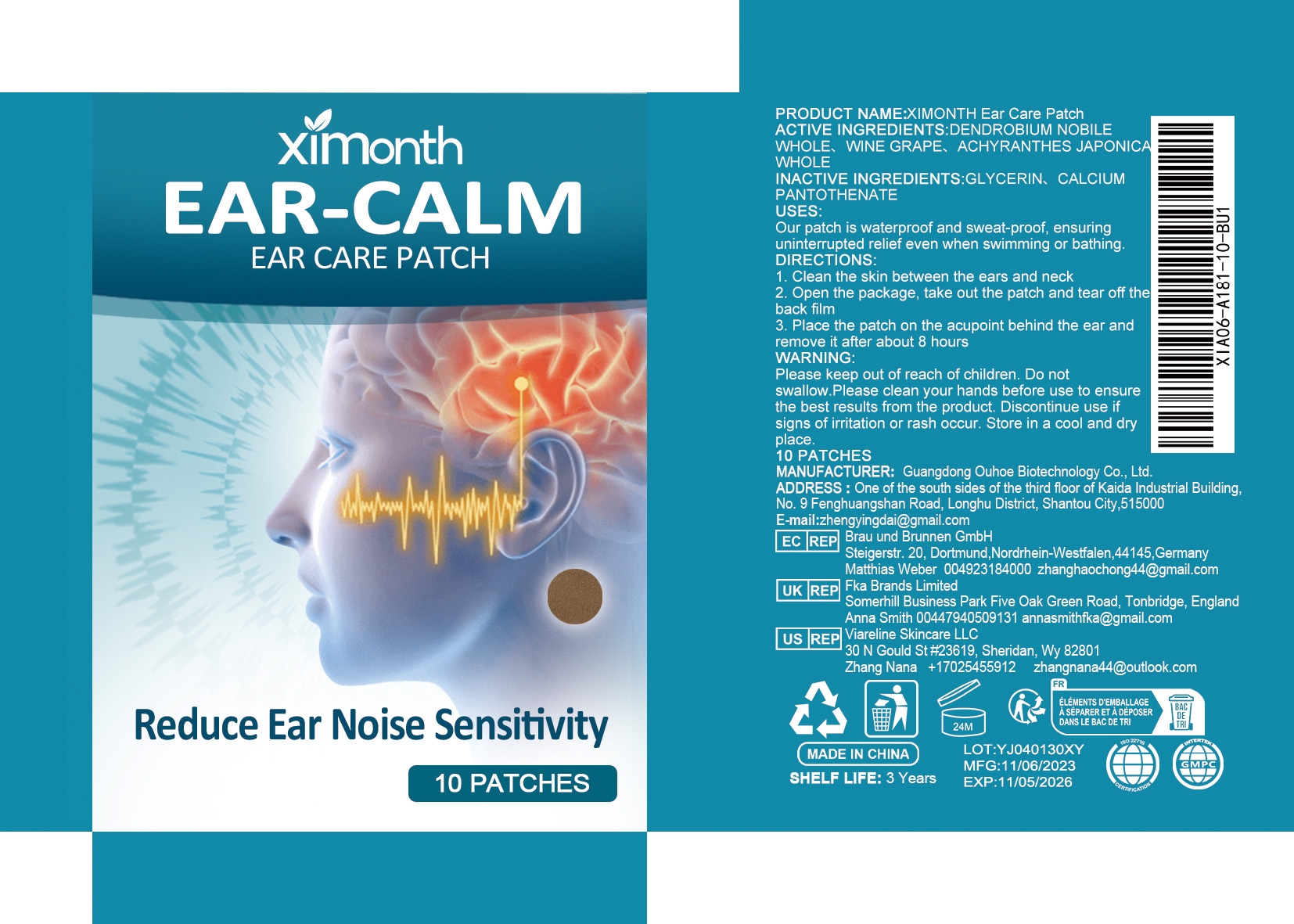 DRUG LABEL: XIMONTH Ear Care Patch
NDC: 84744-008 | Form: PATCH
Manufacturer: Guangdong Ouhoe Biotechnology Co., Ltd.
Category: otc | Type: HUMAN OTC DRUG LABEL
Date: 20241105

ACTIVE INGREDIENTS: DENDROBIUM NOBILE WHOLE 2.1 g/7 g; WINE GRAPE 0.7 g/7 g; ACHYRANTHES JAPONICA WHOLE 1.05 g/7 g
INACTIVE INGREDIENTS: GLYCERIN 1.05 g/7 g; CALCIUM PANTOTHENATE 2.1 g/7 g

ACTIVE INGREDIENTS

DENDROBIUM NOBILE WHOLE、WINE GRAPE、ACHYRANTHES JAPONICA WHOLE

PURPOSE

Our patch is waterproof and sweat-proof, ensuring uninterrupted relief even when swimming or bathing.

USES

1. Clean the skin between the ears and neck2. Open the package, take out the patch and tear off the back film3. Place the patch on the acupoint behind the ear and remove it after about 8 hours

WARNING

Please keep out of reach of children. Do not swallow.Please clean your hands before use to ensure the best results from the product. Discontinue use if signs of irritation or rash occur. Store in a cool and dry place.

STOP USE

Discontinue use if signs of irritation or rash occur.

DO NOT USE

Discontinue use if signs of irritation or rash occur.

KEEP OUT OF REACH OF CHILDREN

Please keep out of reach of children. Do not swallow.

STORAGE AND HANDLING

Store in a cool and dry place.

INACTIVE INGREDIENT

GLYCERIN、CALCIUM PANTOTHENATE